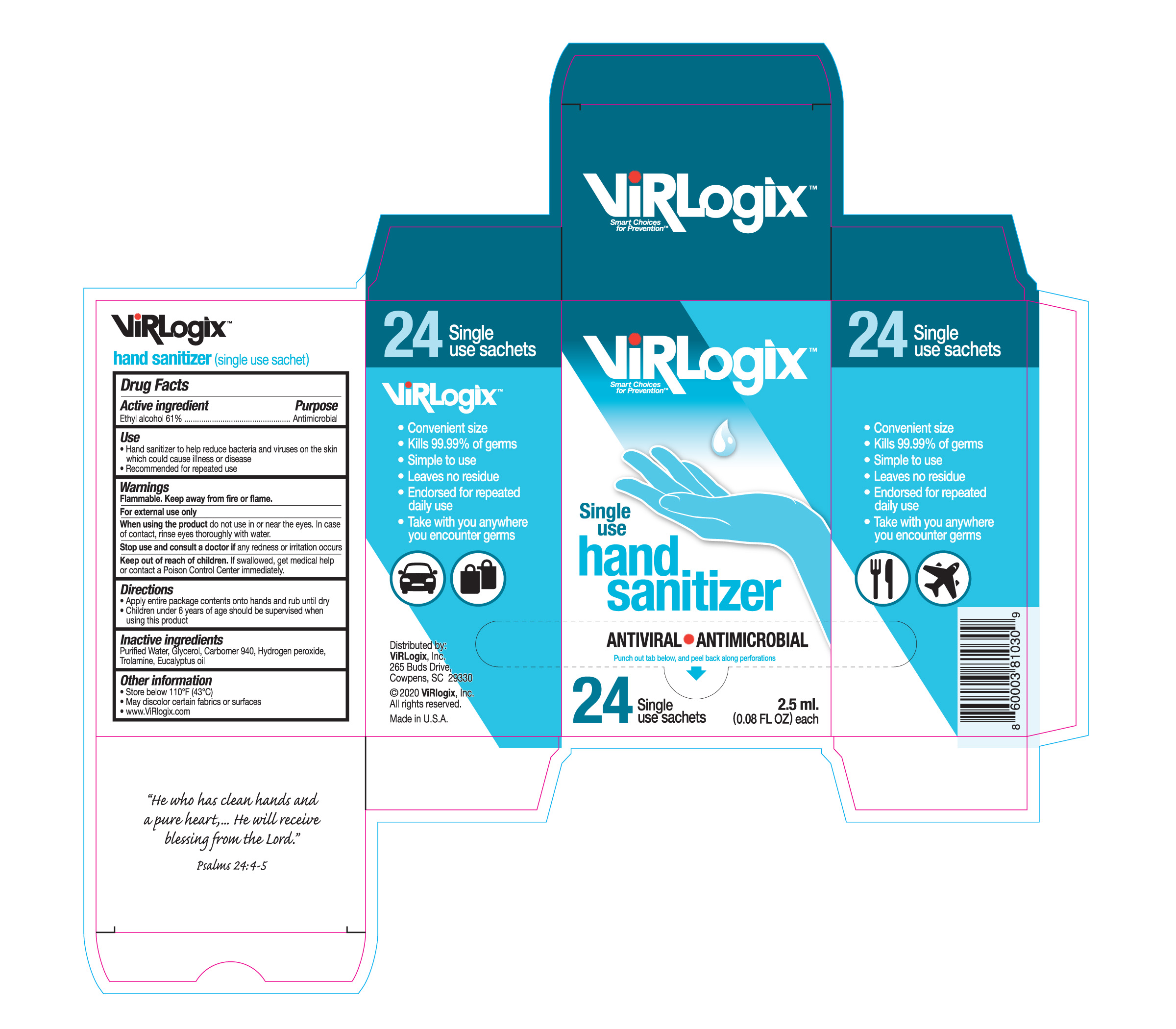 DRUG LABEL: Hand Sanitizer Gel
NDC: 77183-8067 | Form: GEL
Manufacturer: Tekna Fill, Inc.
Category: otc | Type: HUMAN OTC DRUG LABEL
Date: 20200629

ACTIVE INGREDIENTS: ALCOHOL 61 L/100 L
INACTIVE INGREDIENTS: GLYCERIN; HYDROGEN PEROXIDE; WATER; CARBOMER 940; TROLAMINE; EUCALYPTUS OIL

Active Ingredient(s)

Ethyl Alcohol 61% v/v. Purpose: Antimicrobial

Purpose

Antimicrobial, Hand Sanitizer

Use

Hand Sanitizer to help reduce bacteria and viruses on the skin which could cause illness or disease. Recommended for repeated use.

Warnings

Flammable. Keep away from heat or flame.

For external use only

Do not use

- in children less than 2 months of age
- on open skin wounds

When using this product do not use in or near the eyes. In case of contact with eyes, rinse eyes thoroughly with water.
Stop use and ask a doctor if redness or irritation occurs.
Keep out of reach of children. If swallowed, get medical help or contact a Poison Control Center immediately.

Stop use and ask a doctor if irritation or rash occurs. These may be signs of a serious condition.

Keep out of reach of children. If swallowed, get medical help or contact a Poison Control Center immediately.

Directions

- Apply enitre package contents onto hands and rub until dry.
- Children under 6 years of age should be supervised when using this product.

Other information

- Store below 110o F (43o C)
- May discolor certain fabrics or surfaces
- www.ViRlogix.com

Inactive ingredients

Purified Water, Glycerol, Carbomer 940, Hydrogen Peroxide, Trolamine, Eucalyptus Oil

Warnings:

Flammable. Keep away from fire or flame.

For external use only

When using the product do not use in or near the eyes. In case of contact, rinse eyes thoroughtly with water.

Stop use and consult a doctor if redness or irritation occurs.

Keep out of reach of children. If swallowed, get medical helpor contact a Poison Control Center immediately.

Use:

Hand sanitizer to help reduce bacteria and viruses on the skin which could cause illness or disease

Recommeded for repeated use

Directions:

Apply entire package contents onto hands and rub until dry

Children under 6 years of age should be supervised when using this product

Package Label - Principal Display Panel

NDC: 77183-8067-2

24 POUCHES in 1 BOX > .0025L in 1 POUCH